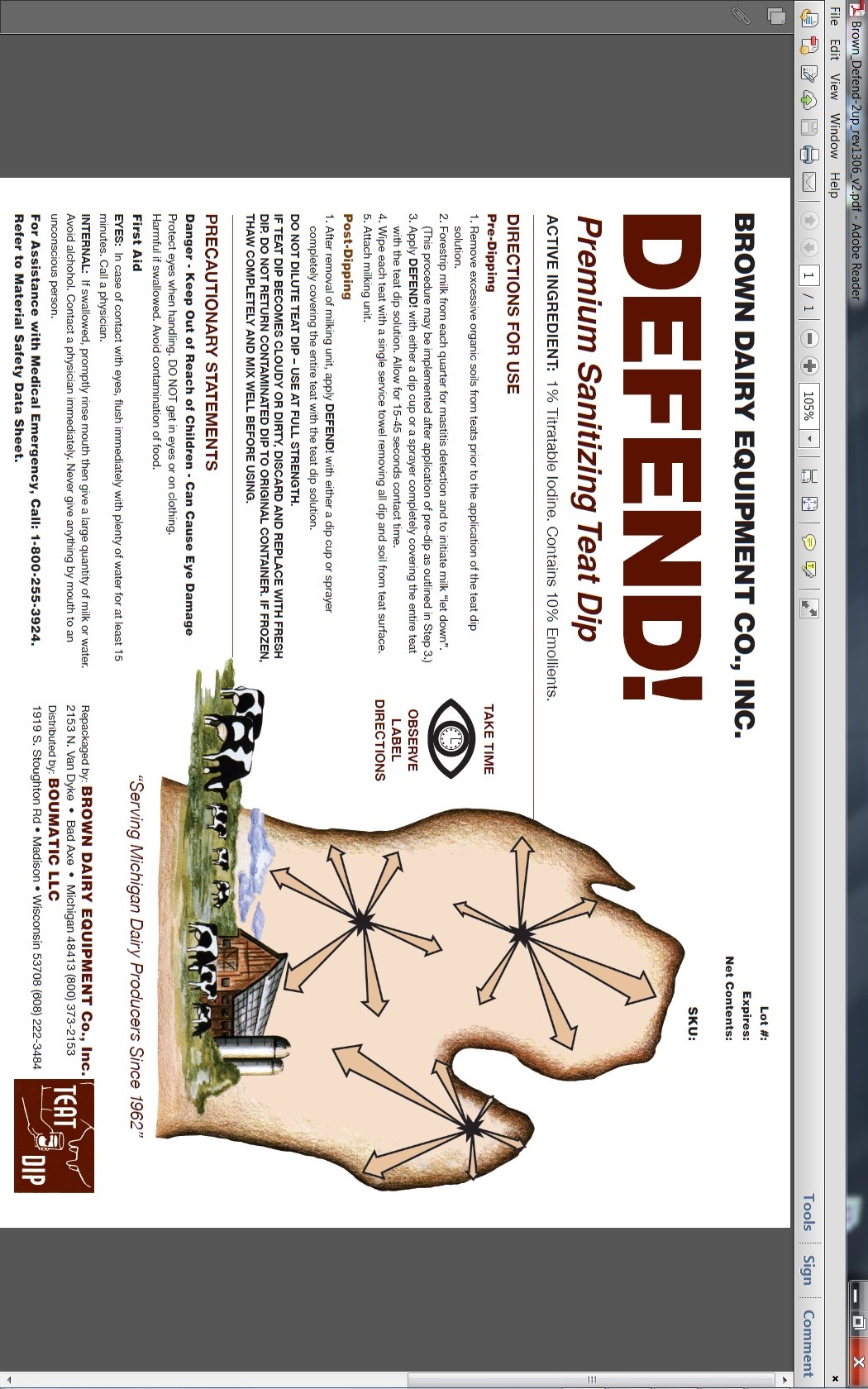 DRUG LABEL: Defend
NDC: 48106-1192 | Form: LIQUID
Manufacturer: BouMatic, LLC
Category: animal | Type: OTC ANIMAL DRUG LABEL
Date: 20120101

ACTIVE INGREDIENTS: IODINE 10 g/1 L

Defend

INDICATIONS AND USAGE

Premium Sanitizing Teat Dip
ACTIVE INGREDIENT: 1% Titratable Iodine. Contains 10% Emollients.

DIRECTIONS FOR USE
Pre-Dipping
1. Remove excessive organic soils from teats prior to the application of the teat dip
solution.
2. Forestrip milk from each quarter for mastitis detection and to initiate milk “let down”. (This procedure may be implemented after application of pre-dip as outlined in Step 3.)
3. Apply DEFEND! with either a dip cup or a sprayer completely covering the entire teat with the teat dip solution. Allow for 15-45 seconds contact time.
4. Wipe each teat with a single service towel removing all dip and soil from teat surface.
5. Attach milking unit.
Post-Dipping
1. After removal of milking unit, apply DEFEND! with either a dip cup or sprayer
completely covering the entire teat with the teat dip solution.
DO NOT DILUTE TEAT DIP – USE AT FULL STRENGTH.
IF TEAT DIP BECOMES CLOUDY OR DIRTY, DISCARD AND REPLACE WITH FRESH DIP. DO NOT RETURN CONTAMINATED DIP TO ORIGINAL CONTAINER.

IF FROZEN, THAW COMPLETELY AND MIX WELL BEFORE USING.

PRECAUTIONS

PRECAUTIONARY STATEMENTS

Danger - Keep Out of Reach of Children - Can Cause Eye Damage
Protect eyes when handling. DO NOT get in eyes or on clothing.
Harmful if swallowed. Avoid contamination of food.
First Aid
EYES: In case of contact with eyes, flush immediately with plenty of water for at least 15 minutes. Call a physician.
INTERNAL: If swallowed, promptly rinse mouth then give a large quantity of milk or water. Avoid alchohol. Contact a physician immediately. Never give anything by mouth to an unconscious person.
For Assistance with Medical Emergency, Call: 1-800-255-3924.
Refer to Material Safety Data Sheet.

PACKAGE LABEL

Enter section text here